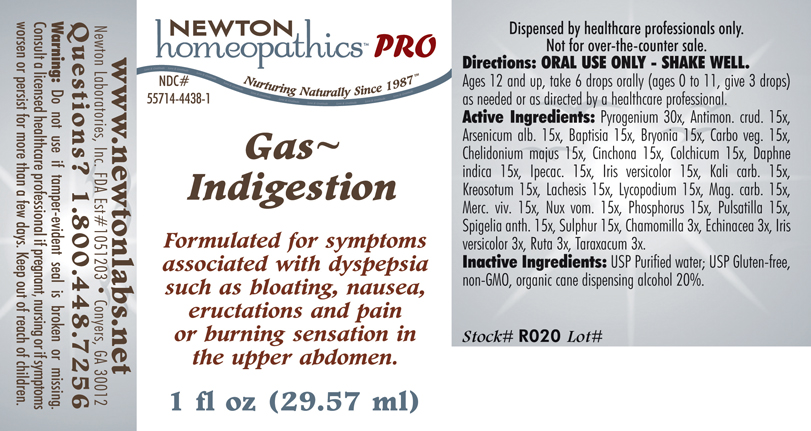 DRUG LABEL: Gas Indigestion 
NDC: 55714-4438 | Form: LIQUID
Manufacturer: Newton Laboratories, Inc.
Category: homeopathic | Type: HUMAN PRESCRIPTION DRUG LABEL
Date: 20110601

ACTIVE INGREDIENTS: Rancid Beef 30 [hp_X]/1 mL; Antimony Trisulfide 15 [hp_X]/1 mL; Arsenic Trioxide 15 [hp_X]/1 mL; Baptisia Tinctoria Root 15 [hp_X]/1 mL; Bryonia Alba Root 15 [hp_X]/1 mL; Activated Charcoal 15 [hp_X]/1 mL; Chelidonium Majus 15 [hp_X]/1 mL; Cinchona Officinalis Bark 15 [hp_X]/1 mL; Colchicum Autumnale Bulb 15 [hp_X]/1 mL; Daphne Odora Bark 15 [hp_X]/1 mL; Ipecac 15 [hp_X]/1 mL; Iris Versicolor Root 15 [hp_X]/1 mL; Potassium Carbonate 15 [hp_X]/1 mL; Wood Creosote 15 [hp_X]/1 mL; Lachesis Muta Venom 15 [hp_X]/1 mL; Lycopodium Clavatum Spore 15 [hp_X]/1 mL; Magnesium Carbonate 15 [hp_X]/1 mL; Mercury 15 [hp_X]/1 mL; Strychnos Nux-vomica Seed 15 [hp_X]/1 mL; Phosphorus 15 [hp_X]/1 mL; Pulsatilla Vulgaris 15 [hp_X]/1 mL; Spigelia Anthelmia 15 [hp_X]/1 mL; Sulfur 15 [hp_X]/1 mL; Matricaria Recutita 3 [hp_X]/1 mL; Echinacea, Unspecified 3 [hp_X]/1 mL; Iris Versicolor Root 3 [hp_X]/1 mL; Ruta Graveolens Flowering Top 3 [hp_X]/1 mL; Taraxacum Officinale 3 [hp_X]/1 mL
INACTIVE INGREDIENTS: Alcohol

Gas Indigestion

PRODUCT NAME & INDICATIONS SECTION

Gas~Indigestion Formulated for symptoms associated with dyspepsia such as bloating, nausea, eructations and pain or burning sensation in the upper abdomen.

DIRECTION SECTION

Directions: ORAL USE ONLY - SHAKE WELL. Ages 12 and up, take 6 drops orally (ages 0 to 11, give 3 drops) as needed or as directed by a healthcare professional.

ACTIVE INGREDIENT SECTION

Pyrogenium 30x, Antimon. crud. 15x, Arsenicum alb. 15x, Baptisia 15x, Bryonia 15x, Carbo veg. 15x, Chelidonium majus 15x, Cinchona 15x, Colchicum 15x, Daphne indica 15x, Ipecac. 15x, Iris versicolor 15x, Kali carb. 15x, Kreosotum 15x, Lachesis 15x, Lycopodium 15x, Mag. carb. 15x, Merc. viv. 15x, Nux vom. 15x, Phosphorus 15x, Pulsatilla 15x, Spigelia anth. 15x, Sulphur 15x, Chamomilla 3x, Echinacea 3x, Iris versicolor 3x, Ruta 3x, Taraxacum 3x.

PURPOSE SECTION

Formulated for symptoms associated with dyspepsia such as bloating, nausea, eructations and pain or burning sensation in the upper abdomen.

INACTIVE INGREDIENT SECTION

Inactive Ingredients: USP Purified Water; USP Gluten-free, non-GMO, organic cane dispensing alcohol 20%.

QUESTIONS? SECTION

www.newtonlabs.net Newton Laboratories, Inc. FDA Est # 1051203 - Conyers, GA 30012
Questions? 1.800.448.7256

WARNINGS SECTION

Warning: Do not use if tamper - evident seal is broken or missing. Consult a licensed healthcare professional if pregnant, nursing or if symptoms worsen or persist for more than a few days. Keep out of reach of children.

OTC - PREGNANCY OR BREAST FEEDING SECTION

Consult a licensed healthcare professional if pregnant, nursing or if symptoms worsen or persist for more than a few days.

OTC - KEEP OUT OF REACH OF CHILDREN SECTION

Keep out of reach of children.